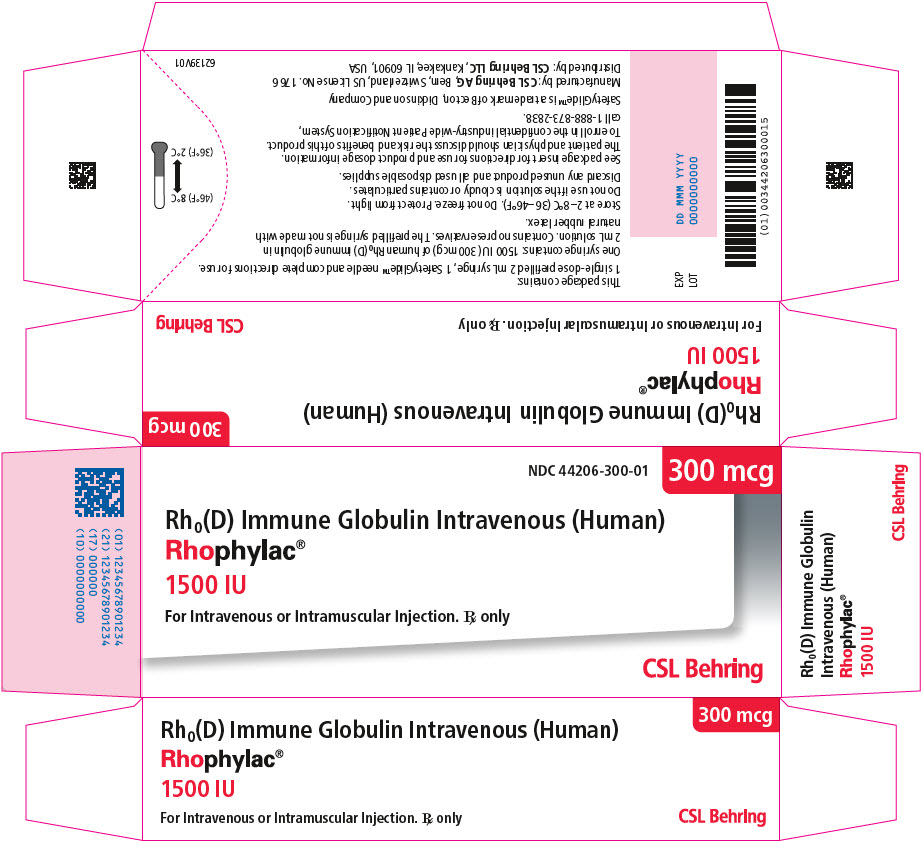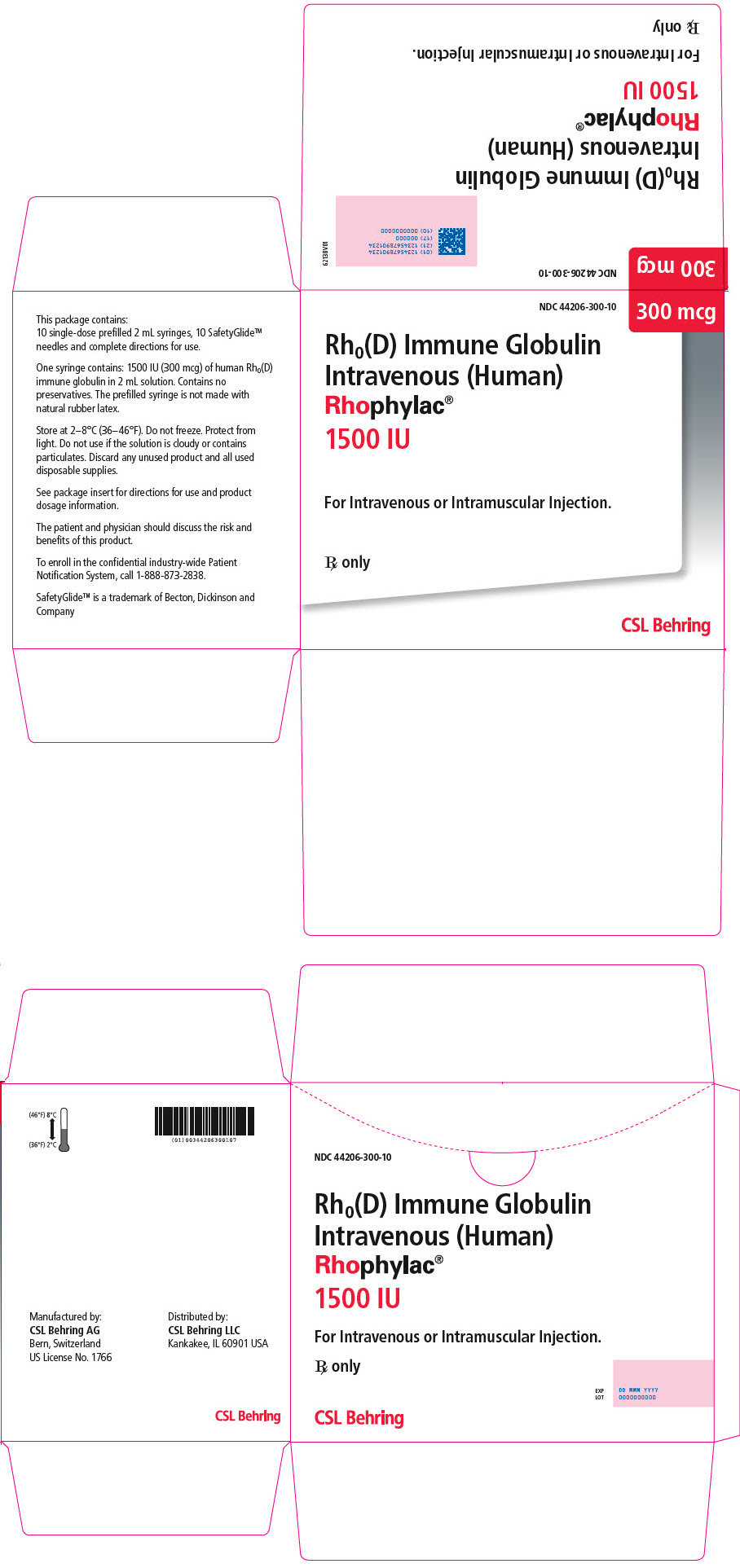 DRUG LABEL: Rhophylac
NDC: 44206-300 | Form: SOLUTION
Manufacturer: CSL Behring AG
Category: other | Type: PLASMA DERIVATIVE
Date: 20250801

ACTIVE INGREDIENTS: HUMAN RHO(D) IMMUNE GLOBULIN 1500 [iU]/2 mL
INACTIVE INGREDIENTS: Albumin Human 20 mg/2 mL; Human Immunoglobulin A; Glycine; Sodium Chloride

HIGHLIGHTS OF PRESCRIBING INFORMATION

These highlights do not include all the information needed to use RHOPHYLAC safely and effectively. See full prescribing information for RHOPHYLAC.
RHOPHYLAC
Rh0(D) Immune Globulin Intravenous (Human) 1500 IU (300 mcg)
Solution for Intravenous (IV) or Intramuscular (IM) Injection
Initial U.S. Approval: 2004

WARNING: INTRAVASCULAR HEMOLYSIS IN ITP

See full prescribing information for complete boxed warning. This warning does not apply to Rh(D)-negative patients treated for the suppression of Rh isoimmunization.

- Intravascular hemolysis leading to death has been reported in Rh (D)-positive patients treated for immune thrombocytopenic purpura (ITP) with Rh(D) Immune Globulin Intravenous (Human) products.
- Intravascular hemolysis can lead to clinically compromising anemia and multi-system organ failure including acute respiratory distress syndrome (ARDS), acute renal insufficiency, renal failure, and disseminated intravascular coagulation (DIC).
- Monitor patients for signs and symptoms of intravascular hemolysis in a healthcare setting for at least 8 hours after administration.

1 INDICATIONS AND USAGE

RHOPHYLAC is a Rh(D) Immune Globulin Intravenous (Human) indicated for:

Suppression of Rhesus (Rh) Isoimmunization (1.1) in:

- Pregnancy and obstetric conditions in non-sensitized, Rh(D)-negative women with an Rh-incompatible pregnancy, including:
  - Routine antepartum and postpartum Rh prophylaxis
  - Rh prophylaxis in obstetric complications or invasive procedures
- Incompatible transfusions in Rh(D)-negative individuals transfused with blood components containing Rh(D)-positive red blood cells (RBCs)

Immune Thrombocytopenic Purpura (ITP) (1.2)

- Raising platelet counts in Rh(D)-positive, non-splenectomized adults with chronic ITP.

2 DOSAGE AND ADMINISTRATION

DO NOT confuse micrograms (mcg) with International Units (IU) when calculating the dose. Miscalculations could result in overdose or underdose

Suppression of Rh Isoimmunization (2.2) (IV or IM administration only)

Indication | Timing | Dose [A 1500 IU (300 mcg) dose will suppress the immunizing potential of ≤15 mL of Rh(D)-positive RBCs.^1] (1 mcg = 5 IU)
Rh-incompatible Pregnancy: |  | mcg | IU
Routine antepartum prophylaxis | Week 28-30 of pregnancy | 300 mcg | 1500 IU
Postpartum prophylaxis (required only if the newborn is Rh(D)-positive, or of unknown status) | Within 72 hours of birth | 300 mcg [The dose must be increased if the patient is exposed to >15 mL of Rh(D)-positive RBCs; in this case, follow the dosing guidelines for excessive fetomaternal hemorrhage.] | 1500 IU
Obstetric complications/invasive procedures | Within 72 hours of complication / procedure | 300 mcg | 1500 IU
Excessive fetomaternal hemorrhage (>15 mL fetal RBCs) | Within 72 hours of complication | 300 mcg plus: 20 mcg per mL RhD-positive fetal RBCs in excess of 15 mL if excess transplacental bleeding is quantified, or An additional 300 mcg if excess transplacental bleeding cannot be quantified | 1500 IU plus: 100 IU per mL RhD- positive fetal RBCs in excess of 15 mL if excess transplacental bleeding is quantified, or An additional 1500 IU if excess transplacental bleeding cannot be quantified
Incompatible transfusions | Within 72 hours of exposure | 20 mcg per 2 mL transfused Rh(D)-positive whole blood or per 1 mL Rh(D)- positive RBCs | 100 IU per 2 mL transfused Rh(D)- positive whole blood or per 1 mL Rh(D)- positive RBCs

Treatment of ITP (2.2) (IV administration only)

Dose (mcg) | Rate of administration
50 mcg per kg body weight | 2 mL per 15 to 60 seconds

3 DOSAGE FORMS AND STRENGTHS

1500 IU (300 mcg) per 2 mL single-dose, prefilled, ready-to-use glass syringe (3)

4 CONTRAINDICATIONS

- History of anaphylactic or severe systemic reaction to human immune globulin products (4)
- IgA deficient patients with antibodies against IgA and a history of hypersensitivity to RHOPHYLAC or any of its components (4)
- Do not administer to the newborn infant of the mother that received RHOPHYLAC postpartum (4).

5 WARNINGS AND PRECAUTIONS

- Hypersensitivity: Severe hypersensitivity and anaphylactic reactions may occur (5.1).
- Transmissible Infectious Agents: Potential of viruses and, theoretically, the Creutzfeldt-Jakob disease (CJD) agent (5.3).
- Intravascular Hemolysis in ITP Treatment: Monitor patients for signs and symptoms and perform confirmatory laboratory tests (5.4).
- Pre-existing Anemia in ITP Treatment: RHOPHYLAC may increase the severity of anemia (5.5).

6 ADVERSE REACTIONS

Suppression of Rh Isoimmunization: Most common adverse reactions in ≥0.5% of subjects are nausea, dizziness, headache, injection-site pain, and malaise (6.1).

ITP: Most common adverse reactions reported in >14% of subjects are chills, pyrexia/increased body temperature, headache, and hemolysis (increased bilirubin, decreased hemoglobin, or decreased haptoglobin) (6.1).

To report SUSPECTED ADVERSE REACTIONS, contact CSL Behring Pharmacovigilance at 1-866-915-6958 or FDA at 1-800-FDA-1088 or www.fda.gov/medwatch.

7 DRUG INTERACTIONS

Immunoglobulin administration may transiently interfere with the immune response to live virus vaccines, such as measles, mumps and rubella (7.1).

FULL PRESCRIBING INFORMATION

RHOPHYLAC®

Rh0(D) Immune Globulin Intravenous (Human)

WARNING: INTRAVASCULAR HEMOLYSIS IN ITP

This warning does not apply to Rh(D)-negative patients treated for the suppression of Rh isoimmunization.

- Intravascular hemolysis leading to death has been reported in Rh(D)-positive patients treated for immune thrombocytopenic purpura (ITP) with Rh(D) Immune Globulin Intravenous (Human) products.
- Intravascular hemolysis can lead to clinically compromising anemia and multi-system organ failure including acute respiratory distress syndrome (ARDS), acute renal insufficiency, renal failure, and disseminated intravascular coagulation (DIC).
- Monitor patients treated for signs and symptoms of hemolysis in a healthcare setting for at least 8 hours after administration. Perform a dipstick urinalysis at baseline, 2 hours and 4 hours after administration, and prior to the end of the monitoring period. Alert patients to, and monitor them for back pain, shaking chills, fever, and discolored urine or hematuria. Absence of these signs and/or symptoms within 8 hours does not indicate IVH cannot occur subsequently. If signs and/or symptoms of intravascular hemolysis are present or suspected after RHOPHYLAC administration, perform post-treatment laboratory tests, including plasma hemoglobin, haptoglobin, LDH, and plasma bilirubin (direct and indirect).

1 INDICATIONS AND USAGE

RHOPHYLAC is a Rh(D) Immune Globulin Intravenous (Human) (anti-D) product that is indicated for the suppression of Rh isoimmunization in non-sensitized Rh(D)-negative patients and for the treatment of immune thrombocytopenic purpura (ITP) in Rh(D)-positive patients.

1.1 Suppression of Rh Isoimmunization

Pregnancy and Obstetric Conditions

RHOPHYLAC is indicated for suppression of rhesus (Rh) isoimmunization in non-sensitized Rh(D)-negative women with an Rh-incompatible pregnancy, including:

- Routine antepartum and postpartum Rh prophylaxis
- Rh prophylaxis in cases of:
  1. Obstetric complications (e.g., miscarriage, abortion, threatened abortion, ectopic pregnancy or hydatidiform mole, transplacental hemorrhage resulting from antepartum hemorrhage)
  2. Invasive procedures during pregnancy (e.g., amniocentesis, chorionic biopsy) or obstetric manipulative procedures (e.g., external version, abdominal trauma)

An Rh-incompatible pregnancy is assumed if the fetus/baby is either Rh(D)-positive or Rh(D)-unknown or if the father is either Rh(D)-positive or Rh(D)-unknown.

Incompatible Transfusions

RHOPHYLAC is indicated for the suppression of Rh isoimmunization in Rh(D)-negative individuals transfused with Rh(D)-positive red blood cells (RBCs) or blood components containing Rh(D)-positive RBCs.

Treatment can be given without a preceding exchange transfusion when the transfused blood represents less than 20% of the total circulating RBCs. If the volume exceeds 20%, an exchange transfusion should be considered prior to administering RHOPHYLAC.

1.2 ITP

RHOPHYLAC is indicated in Rh(D)-positive, non-splenectomized adult patients with chronic ITP to raise platelet counts.

2 DOSAGE AND ADMINISTRATION

Observe patients for at least 20 minutes following administration of RHOPHYLAC.

2.1 Preparation and Handling

- RHOPHYLAC is a clear or slightly opalescent, colorless to pale yellow solution. Inspect RHOPHYLAC visually for particulate matter and discoloration prior to administration. Do not use if the solution is cloudy or contains particulates.
- Prior to intravenous use, ensure that the needle-free intravenous administration system is compatible with the tip of the RHOPHYLAC glass syringe.
- Do not freeze.
- Bring RHOPHYLAC to room temperature before use.
- RHOPHYLAC is for single dose only. Dispose of any unused product or waste material in accordance with local requirements.

2.2 Administration

DO NOT confuse micrograms (mcg) with International Units (IU) when calculating the dose of RHOPHYLAC. Miscalculations could result in a significant overdose or underdose of the product. Note that 1 mcg = 5 IU of RHOPHYLAC.

Suppression of Rh Isoimmunization

RHOPHYLAC should be administered by intravenous or intramuscular injection. If large doses (greater than 5 mL) are required and intramuscular injection is chosen, it is advisable to administer RHOPHYLAC in divided doses at different sites.

Ensure the site of administration will allow the injection to reach the muscle if RHOPHYLAC is administered intramuscularly. Consider intravenous administration if reaching the muscle is of concern [see Adverse Reactions (6.2)]. Do not administer RHOPHYLAC subcutaneously into the fatty tissue.

Refer to Table 1 (for dosing instructions in micrograms) and Table 2 (for dosing instructions in International Units) by indication.

Table 1. Dosing Guidelines based on Micrograms (mcg) for Suppression of Rh Isoimmunization
MICROGRAMS (mcg)
Indication | Timing of Administration | Dose [A 300 mcg dose of RHOPHYLAC will suppress the immunizing potential of ≤15 mL of fetal Rh(D)-positive RBCs.^1] (Administer by intravenous (IV) or intramuscular (IM) injection)
Rh-incompatible pregnancy
Routine antepartum prophylaxis | Week 28-30 of pregnancy | 300 mcg
Postpartum prophylaxis (required only if the newborn is Rh(D)-positive, or of unknown status) | Within 72 hours of birth | 300 mcg [The dose of RHOPHYLAC must be increased if the patient is exposed to >15 mL of fetal Rh(D)-positive RBCs; in this case, follow the dosing guidelines for excessive fetomaternal hemorrhage.]
Obstetric complications (e.g., miscarriage, abortion, threatened abortion, ectopic pregnancy or hydatidiform mole, transplacental hemorrhage resulting from antepartum hemorrhage) | Within 72 hours of complication | 300 mcg
Invasive procedures during pregnancy (e.g., amniocentesis, chorionic biopsy) or obstetric manipulative procedures (e.g., external version, abdominal trauma) | Within 72 hours of procedure | 300 mcg
Excessive fetomaternal hemorrhage (>15 mL fetal RBCs) | Within 72 hours of complication | 300 mcg plus:; - 20 mcg per mL Rh(D)-positive fetal RBCs in excess of 15 mL if excess transplacental bleeding is quantified or - An additional 300 mcg dose if excess transplacental bleeding cannot be quantified
Incompatible transfusions | Within 72 hours of exposure | 20 mcg per 2 mL transfused Rh(D)-positive whole blood or per 1 mL Rh(D)-positive RBCs

Table 2. Dosing Guidelines based on International Units (IU) for Suppression of Rh Isoimmunization
INTERNATIONAL UNITS (IU)
Indication | Timing of Administration | Dose [A 1500 IU dose of RHOPHYLAC will suppress the immunizing potential of ≤15 mL of fetal Rh(D)-positive RBCs.^1] (Administer by intravenous (IV) or intramuscular (IM) injection)
Rh-incompatible pregnancy
Routine antepartum prophylaxis | Week 28-30 of pregnancy | 1500 IU
Postpartum prophylaxis (required only if the newborn is Rh(D)-positive, or of unknown status) | Within 72 hours of birth | 1500 IU [The dose of RHOPHYLAC must be increased if the patient is exposed to >15 mL of fetal Rh(D)-positive RBCs; in this case, follow the dosing guidelines for excessive fetomaternal hemorrhage.]
Obstetric complications (e.g., miscarriage, abortion, threatened abortion, ectopic pregnancy or hydatidiform mole, transplacental hemorrhage resulting from antepartum hemorrhage) | Within 72 hours of complication | 1500 IU
Invasive procedures during pregnancy (e.g., amniocentesis, chorionic biopsy) or obstetric manipulative procedures (e.g., external version, abdominal trauma) | Within 72 hours of procedure | 1500 IU
Excessive fetomaternal hemorrhage (>15 mL fetal RBCs) | Within 72 hours of complication | 1500 IU plus:; - 100 IU per mL fetal RBCs in excess of 15 mL if excess transplacental bleeding is quantified or - An additional 1500 IU dose if excess transplacental bleeding cannot be quantified
Incompatible transfusions | Within 72 hours of exposure | 100 IU per 2 mL transfused Rh(D)- positive whole blood or per 1 mL RBCs

Treatment of ITP

For treatment of ITP, ADMINISTER RHOPHYLAC BY THE INTRAVENOUS ROUTE ONLY [see Dosage and Administration (2.1)]. Do not administer intramuscularly.

Calculate the dose of RHOPHYLAC for ITP on the basis of the patient's weight in kilograms (kg). Inappropriate use of pounds (lbs) will result in an overdose.

Table 3. Dosing Guidelines for ITP
Dose (mcg) |  | Rate of administration
50 mcg per kg body weight |  | 2 mL per 15 to 60 seconds
mcg = microgram

The following formula can be used to calculate the number of syringes of RHOPHYLAC to administer:

Dose (50 mcg) x body weight (kg) = Total mcg / 300 mcg per syringe = Number of syringes

3 DOSAGE FORMS AND STRENGTHS

1500 IU (300 mcg) per 2 mL single-dose, prefilled, ready-to-use, glass syringe for IV or IM use

4 CONTRAINDICATIONS

RHOPHYLAC is contraindicated in:

- patients who have had an anaphylactic or severe systemic reaction to the administration of human immune globulin,
- IgA-deficient patients with antibodies to IgA and a history of hypersensitivity to RHOPHYLAC or any of its components,
- the newborn infant of a mother that received RHOPHYLAC postpartum.

5 WARNINGS AND PRECAUTIONS

5.1 Hypersensitivity

Severe hypersensitivity reactions may occur even in patients who have tolerated previous administrations. If symptoms of allergic or early signs of hypersensitivity reactions (including generalized urticaria, tightness of the chest, wheezing, hypotension, and anaphylaxis) occur, discontinue RHOPHYLAC administration immediately and institute appropriate treatment. Medications such as epinephrine should be available for immediate treatment of acute hypersensitivity reactions.

RHOPHYLAC contains trace amounts of IgA (less than 5 mcg/mL) [see Description (11)]. Patients with known antibodies to IgA have a risk of developing potentially severe hypersensitivity and anaphylactic reactions. RHOPHYLAC is contraindicated in patients with antibodies against IgA and a history of hypersensitivity reactions to RHOPHYLAC or any of its components [see Contraindications (4)].

5.2 Interference with Laboratory Tests

The administration of Rh (D) immune globulin may affect the results of blood typing, the antibody screening test, and the direct antiglobulin (Coombs') test. Antepartum administration of Rh(D) immune globulin to the mother can also affect these tests in the newborn infant.

RHOPHYLAC can contain antibodies to other Rh antigens (e.g., anti-C antibodies), which might be detected by sensitive serological tests following administration.

5.3 Transmissible Infectious Agents

Because RHOPHYLAC is made from human blood, it may carry a risk of transmitting infectious agents, e.g., viruses and, theoretically, the Creutzfeldt-Jakob disease (CJD) agent. The risk of infectious agent transmission has been reduced by screening plasma donors for prior exposure to certain viruses, testing for the presence of certain current virus infections, and including virus inactivation/removal steps in the manufacturing process for RHOPHYLAC.

Report any infections thought to be possibly transmitted by RHOPHYLAC to CSL Behring Pharmacovigilance at 1-866-915-6958.

5.4 Intravascular Hemolysis in ITP Treatment

Serious intravascular hemolysis has occurred in a clinical study with RHOPHYLAC. All cases resolved completely. However, as reported in the literature, some Rh(D)-positive patients treated with Rh(D) Immune Globulin Intravenous (Human) for ITP developed clinically compromising anemia, acute renal insufficiency, and, very rarely, disseminated intravascular coagulation (DIC) and death.^2 Note: This warning does not apply to Rh(D)-negative patients treated for the suppression of Rh isoimmunization.

Monitor patients in a healthcare setting for at least 8 hours after administration of RHOPHYLAC. Perform a dipstick urinalysis at baseline, 2 hours and 4 hours after administration, and prior to the end of the monitoring period.

Alert patients to, and monitor them for, the signs and symptoms of intravascular hemolysis, including back pain, shaking chills, fever, and discolored urine or hematuria. Absence of these signs and/or symptoms of intravascular hemolysis within 8 hours do not indicate intravascular hemolysis cannot occur subsequently.

If signs and/or symptoms of intravascular hemolysis are present or suspected after RHOPHYLAC administration, perform post-treatment laboratory tests, including plasma hemoglobin, haptoglobin, LDH, and plasma bilirubin (direct and indirect). DIC may be difficult to detect in the ITP population; the diagnosis is dependent mainly on laboratory testing.

If patients who develop hemolysis with clinically compromising anemia after receiving RHOPHYLAC are to be transfused, Rh(D)-negative packed RBCs should be used to avoid exacerbating ongoing hemolysis.

5.5 Pre-existing Anemia in ITP Treatment

The safety of RHOPHYLAC in the treatment of ITP has not been established in patients with pre-existing anemia. RHOPHYLAC may increase the severity of anemia.

6 ADVERSE REACTIONS

The most serious adverse reactions in patients receiving Rh(D) Immune Globulin Intravenous (Human) have been observed in the treatment of ITP and include intravascular hemolysis, clinically compromising anemia, acute renal insufficiency, and, very rarely, DIC and death [see Boxed Warning, and Warnings and Precautions (5.4)].^2

The most common adverse reactions observed with the use of RHOPHYLAC for suppression of Rh isoimmunization (≥0.5% of subjects) are nausea, dizziness, headache, injection-site pain, and malaise.

The most common adverse reactions observed in the treatment of ITP (>14% of subjects) are chills, pyrexia/increased body temperature, and headache. Hemolysis (manifested by an increase in bilirubin, a decrease in hemoglobin, or a decrease in haptoglobin) was also observed.

6.1 Clinical Trials Experience

Because clinical studies are conducted under different protocols and widely varying conditions, adverse reaction rates observed cannot be directly compared to rates in other clinical trials and may not reflect the rates observed in practice.

Suppression of Rh Isoimmunization

In two clinical studies, 447 Rh(D)-negative pregnant women received either an intravenous or intramuscular injection of RHOPHYLAC 1500 IU (300 mcg) at Week 28 of gestation. A second 1500 IU (300 mcg) dose was administered to 267 (9 in Study 1 and 258 in Study 2) of these women within 72 hours of the birth of an Rh(D)-positive baby. In addition, 30 women in Study 2 received at least one extra antepartum 1500 IU (300 mcg) dose due to obstetric complications [see Clinical Studies (14.1)].

The most common adverse reactions in study subjects were nausea (0.7%), dizziness (0.5%), headache (0.5%), injection-site pain (0.5%), and malaise (0.5%). A laboratory finding of a transient positive anti-C antibody test was observed in 0.9% of subjects.

ITP

In a clinical study, 98 Rh(D)-positive adult subjects with chronic ITP received an intravenous dose of RHOPHYLAC 250 IU (50 mcg) per kg body weight [see Clinical Studies (14.2)]. Premedication to alleviate infusion-related side effects was not used except in a single subject who received acetaminophen and diphenhydramine.

Sixty-nine (70.4%) subjects had 186 adverse events. Within 24 hours of dosing, 73 (74.5%) subjects experienced 183 Treatment Emergent Adverse Events, and 66 (67%) subjects experienced 156 adverse reactions.

Hemolysis (manifested as an increase in bilirubin, a decrease in hemoglobin, or a decrease in haptoglobin) was observed. An increase in blood bilirubin was seen in 21% of subjects. The median decrease in hemoglobin was greatest (0.8 g/dL) at Day 6 and Day 8 following administration of RHOPHYLAC.

Table 4 shows the most common adverse reactions observed in the clinical study.

Table 4. Most Common Treatment-Emergent Adverse Reactions in Subjects with ITP (Occurring in ≥10% of Subjects)
TEAR | Number of Subjects (%) With a TEAR n=98
Chills | 34 (34.7%)
Pyrexia/ Increased body temperature | 30 (30.6%)
Increased blood bilirubin | 21 (21.4%)
Headache | 11 (11.2%)

Serious adverse reactions (SARs) were reported in 4 (4.1%) subjects. SARs were intravascular hemolytic reaction (hypotension, nausea, chills and headache, and a decrease in haptoglobin and hemoglobin) in two subjects; headache, dizziness, nausea, pallor, shivering, and weakness requiring hospitalization in one subject; and an increase in blood pressure and severe headache in one subject. All four subjects recovered completely.

6.2 Postmarketing Experience

Because postmarketing adverse reactions are reported voluntarily from a population of uncertain size, it is not always possible to reliably estimate their frequency or establish a causal relationship to product exposure. The following adverse reactions have been identified during post-approval use of RHOPHYLAC:

Suppression of Rh Isoimmunization

Hypersensitivity reactions, including rare cases of anaphylactic shock or anaphylactoid reactions, headache, dizziness, vertigo, hypotension, tachycardia, dyspnea, nausea, vomiting, rash, erythema, pruritus, chills, pyrexia, malaise, diarrhea and back pain have been reported. Transient injection-site irritation and pain have been observed following intramuscular administration.

There have been reports of lack of effect in patients with a body mass index ≥30 when administration via the intramuscular route was attempted [see Dosing and Administration (2.2)].

ITP

Transient hemoglobinuria has been reported in a patient being treated with RHOPHYLAC for ITP.

7 DRUG INTERACTIONS

7.1 Live Virus Vaccines

Passive transfer of antibodies may transiently impair the immune response to live attenuated virus vaccines such as measles, mumps, rubella, and varicella [see Patient Counseling Information (17)]. Do not immunize with live vaccines within 3 months after the final dose of RHOPHYLAC. If RHOPHYLAC is administered within 14 days after administration of a live vaccine, the immune response to the vaccination may be inhibited.^3

8 USE IN SPECIFIC POPULATIONS

8.1 Pregnancy

Risk Summary

Animal reproduction studies have not been conducted with Rhophylac.

Suppression of Rh Isoimmunization

RHOPHYLAC is used in pregnant women for the suppression of Rh isoimmunization. When administered to pregnant women in a clinical trial to evaluate RHOPHYLAC for suppression of Rh isoimmunization [see Clinical Studies (14.1)] following dosing regimens similar to Table 1 or 2 [see Dosage and Administration (2.2)], RHOPHYLAC was not shown to harm the fetus or newborn.^11 In general, anti-D immunoglobulins have been shown to not harm the fetus or affect future pregnancies or reproduction capacity when given to pregnant Rh(D)-negative women for suppression of Rh isoimmunization.^4

ITP

RHOPHYLAC has not been evaluated in pregnant women with ITP.

In the U.S. general population, the estimated background risk of major birth defects and miscarriage in clinically recognized pregnancies is 2-4% and 15-20%, respectively.

8.2 Lactation

Risk Summary

There is no information regarding the presence of RHOPHYLAC in human milk, the effect on the breastfed infant, and the effects on milk production. The development and health benefits of breastfeeding should be considered along with the mother's clinical need for RHOPHYLAC and any potential adverse effects on the breastfed child from RHOPHYLAC or from the underlying maternal condition.

Suppression of Rh Isoimmunization

RHOPHYLAC is used in nursing mothers for the suppression of Rh isoimmunization.

ITP

RHOPHYLAC has not been evaluated in nursing mothers with ITP.

8.4 Pediatric Use

Suppression of Rh Isoimmunization in Incompatible Transfusions

The safety and effectiveness of RHOPHYLAC have not been established in pediatric subjects being treated for an incompatible transfusion. The physician should weigh the potential risks against the benefits of RHOPHYLAC, particularly in girls whose later pregnancies may be affected if Rh isoimmunization occurs.

Chronic ITP

The safety and effectiveness of RHOPHYLAC have not been established in pediatric subjects with chronic ITP. Dosing in the treatment of children with chronic ITP is expected to be similar to adults.

8.5 Geriatric Use

Suppression of Rh Isoimmunization in Incompatible Transfusions

RHOPHYLAC has not been evaluated for treating incompatible transfusions in subjects 65 years of age and older.

ITP

Of the 98 subjects evaluated in the clinical study of RHOPHYLAC for treatment of ITP [see Clinical Studies (14.2)], 19% were 65 years of age and older. No overall differences in effectiveness or safety were observed between these subjects and younger subjects.

10 OVERDOSAGE

During clinical trials, there were no reports of known overdoses in patients being treated for suppression of Rh isoimmunization or ITP. In postmarketing reporting, there have been a limited number of overdose reports including medication error reports related to dosage calculations in which higher doses than that recommended for RHOPHYLAC were administered potentially due to confusion between mcg and international units (IU). In these reports there were no adverse reactions identified due to overdose. Patients with incompatible transfusion or ITP who receive an overdose of Rh(D) immune globulin should be monitored because of the potential risk for hemolysis.

11 DESCRIPTION

RHOPHYLAC is a sterile Rh(D) Immune Globulin Intravenous (Human) (anti-D) solution in a ready-to-use prefilled glass syringe for intravenous or intramuscular injection. One syringe contains at least 1500 IU (300 mcg) of IgG antibodies to Rh(D) in a 2 mL solution, sufficient to suppress the immune response to at least 15 mL of Rh(D)-positive RBCs.^1 The product potency is expressed in IUs by comparison to the World Health Organization (WHO) standard, which is also the US and the European Pharmacopoeia standard.

Plasma is obtained from healthy Rh(D)-negative donors who have been immunized with Rh(D)-positive RBCs. The donors are screened carefully to reduce the risk of receiving donations containing blood-borne pathogens. Each plasma donation used in the manufacture of RHOPHYLAC is tested for the presence of HBV surface antigen (HBsAg), HIV-1/2, and HCV antibodies. In addition, plasma used in the manufacture of RHOPHYLAC is tested by FDA-licensed Nucleic Acid Testing (NAT) for HBV, HCV, and HIV-1 and found to be negative. The source plasma is also tested by NAT for hepatitis A virus (HAV) and B19 virus (B19V).

RHOPHYLAC is produced by an ion-exchange chromatography isolation procedure^5, using pooled plasma obtained by plasmapheresis of immunized Rh(D)-negative US donors.

The manufacturing process of RHOPHYLAC includes two dedicated virus reduction steps (i.e., solvent/detergent treatment and virus filtration with a Planova® 15 nanometer (nm) virus filter) as well as one ion exchange chromatography step contributing to virus reduction.^6,7 All three virus reduction steps have been independently validated in a series of in vitro experiments for their capacity to inactivate or remove enveloped and/or non-enveloped viruses. Virus models were chosen to cover a broad selection of viruses, including the major blood-transmissible viruses like human immunodeficiency virus, hepatitis B and hepatitis C virus, as well as small, non-enveloped viruses like hepatitis A virus and human parvovirus B19. Viral clearance data from validation studies of the dedicated virus reduction steps for both enveloped and nonenveloped viruses will be provided upon request by calling 1-800-504-5434. Overall virus reduction expressed as mean log10 reduction factor of model enveloped and non-enveloped viruses has been shown to be ≥11 log10 and ≥9 log10 respectively.

RHOPHYLAC contains a maximum of 30 mg/mL of human plasma proteins, 10 mg/mL of which is human albumin added as a stabilizer. Prior to the addition of the stabilizer, RHOPHYLAC has a purity greater than 95% IgG. RHOPHYLAC contains less than 5 mcg/mL of IgA, which is the limit of detection. Additional excipients are approximately 20 mg/mL of glycine and up to 0.25 M of sodium chloride. RHOPHYLAC contains no preservative. Human albumin is manufactured from pooled plasma of US donors by cold ethanol fractionation, followed by pasteurization.

12 CLINICAL PHARMACOLOGY

12.1 Mechanism of Action

Suppression of Rh Isoimmunization

The mechanism by which Rh(D) immune globulin suppresses immunization to Rh(D)-positive RBCs is not completely known.

In a clinical study of Rh(D)-negative healthy male volunteers, both the intravenous and intramuscular administration of a 1500 IU (300 mcg) dose of RHOPHYLAC 24 hours after injection of 15 mL of Rh(D)-positive RBCs resulted in an effective clearance of Rh(D)-positive RBCs. On average, 99% of injected RBCs were cleared within 12 hours following intravenous administration and within 144 hours following intramuscular administration.

ITP

RHOPHYLAC has been shown to increase platelet counts and to reduce bleeding in non-splenectomized Rh(D)-positive subjects with chronic ITP. The mechanism of action is thought to involve the formation of Rh(D) immune globulin RBC complexes, which are preferentially removed by the reticuloendothelial system, particularly the spleen. This results in Fc receptor blockade, thus sparing antibody-coated platelets.^8

12.3 Pharmacokinetics

Suppression of Rh Isoimmunization

In a clinical study comparing the pharmacokinetics of intravenous versus intramuscular administration, 15 Rh(D)-negative pregnant women received a single 1500 IU (300 mcg) dose of RHOPHYLAC at Week 28 of gestation.^9

Following intravenous administration, peak serum levels of Rh(D) immune globulin ranged from 62 to 84 ng/mL after 1 day (i.e., the time the first blood sample was taken following the antepartum dose). Mean systemic clearance was 0.20 ± 0.03 mL/min, and half-life was 16 ± 4 days.

Following intramuscular administration, peak serum levels ranged from 7 to 46 ng/mL and were achieved between 2 and 7 days. Mean apparent clearance was 0.29 ± 0.12 mL/min, and half-life was 18 ± 5 days. The absolute bioavailability of RHOPHYLAC was 69%.

Regardless of the route of administration, Rh(D) immune globulin titers were detected in all women up to at least 9 weeks following administration of RHOPHYLAC.

ITP

Pharmacokinetic studies with RHOPHYLAC were not performed in Rh(D)-positive subjects with ITP. Rh(D) immune globulin binds rapidly to Rh(D)-positive erythrocytes.^10

14 CLINICAL STUDIES

14.1 Suppression of Rh Isoimmunization

In two clinical studies, 447 Rh(D)-negative pregnant women received a 1500 IU (300 mcg) dose of RHOPHYLAC during Week 28 of gestation. The women who gave birth to an Rh(D)-positive baby received a second 1500 IU (300 mcg) dose within 72 hours of birth.

- Study 1 (Pharmacokinetic Study) – Eight of the women who participated in the pharmacokinetic study [see Clinical Pharmacology (12.3)] gave birth to an Rh(D)-positive baby and received the postpartum dose of 1500 IU (300 mcg) of RHOPHYLAC.^9 Antibody tests performed 6 to 8 months later were negative for all women. This suggests that no Rh(D) immunization occurred.
- Study 2 (Pivotal Study) – In an open-label, single-arm clinical study at 22 centers in the US and United Kingdom, 432 pregnant women received the antepartum dose of 1500 IU (300 mcg) of RHOPHYLAC either as an intravenous or intramuscular injection (two randomized groups of 216 women each).^11 Subjects received an additional 1500 IU (300 mcg) dose if an obstetric complication occurred between the routine antepartum dose and birth or if extensive fetomaternal hemorrhage was measured after birth. Of the 270 women who gave birth to an Rh(D)-positive baby, 248 women were evaluated for Rh(D) immunization 6 to 11.5 months postpartum. None of these women developed antibodies against the Rh(D) antigen.

14.2 ITP

In an open-label, single-arm, multicenter study, 98 Rh(D)-positive adult subjects with chronic ITP and a platelet count of 30 × 10^9/L or less were treated with RHOPHYLAC. Subjects received a single intravenous dose of 250 IU (50 mcg) per kg body weight.

The primary efficacy endpoint was the response rate defined as achieving a platelet count of ≥30 × 10^9/L as well as an increase of >20 × 10^9/L within 15 days after treatment with RHOPHYLAC. Secondary efficacy endpoints included the response rate defined as an increase in platelet counts to ≥50 × 10^9/L within 15 days after treatment and, in subjects who had bleeding at baseline, the regression of hemorrhage defined as any decrease from baseline in the severity of overall bleeding status.

Table 5 presents the primary response rates for the intent-to-treat (ITT) and per-protocol (PP) populations.

Table 5. Primary Response Rates (ITT and PP Populations)
 |  |  | Primary Response Rate at Day 15
Analysis Population | No. Subjects | No. Responders | % Responders | 95% Confidence Interval (CI)
ITT | 98 | 65 | 66.3% | 56.5%, 74.9%
PP | 92 | 62 | 67.4% | 57.3%, 76.1%

The primary efficacy response rate (ITT population) demonstrated a clinically relevant response to treatment, i.e., the lower bound of the 95% confidence interval (CI) was greater than the predefined response rate of 50%. The median time to platelet response was 3 days, and the median duration of platelet response was 22 days.

Table 6 presents the response rates by baseline platelet count for subjects in the ITT population.

Table 6. Response Rates by Baseline Platelet Count (ITT Population)
 |  | Response Rates at Day 15
Baseline Platelet count (× 10^9/L) | Total No. Subjects | No. (%) Subjects Achieving a Platelet Count of ≥30 × 10^9/L and an Increase of >20 × 10^9/L | No. (%) Subjects With an Increase in Platelet Counts to ≥50 × 10^9/L
≤10 | 38 | 15 (39.5) | 10 (26.3)
>10 to 20 | 28 | 22 (78.6) | 17 (60.7)
>20 to 30 | 27 | 24 (88.9) | 22 (81.5)
>30 [Reflects subjects with a platelet count of ≤30 × 10^9/L at screening but >30 × 10^9/L immediately before treatment.] | 5 | 4 (80.0) | 5 (100.0)
Overall (all subjects) | 98 | 65 (66.3) | 54 (55.1)

During the study, an overall regression of hemorrhage was seen in 44 (88%, 95% CI: 76% to 94%) of the 50 subjects with bleeding at baseline. The percentage of subjects showing a regression of hemorrhage increased from 20% at Day 2 to 64% at Day 15. There was no evidence of an association between the overall hemorrhage regression rate and baseline platelet count.

Approximately half of the 98 subjects in the ITT population had evidence of bleeding at baseline. Post-baseline, the percentage of subjects without bleeding increased to a maximum of 70.4% at Day 8.

15 REFERENCES

1. Pollack W, Ascari WQ, Kochesky RJ, O'Connor RR, Ho TY, Tripodi D. Studies on Rh prophylaxis. 1. relationship between doses of anti-Rh and size of antigenic stimulus. Transfusion. 1971;11:333-339.
2. Gaines AR. Disseminated intravascular coagulation associated with acute hemoglobinemia or hemoglobinuria following Rh0(D) immune globulin intravenous administration for immune thrombocytopenic purpura. Blood. 2005;106:1532-1537.
3. Centers for Disease Control and Prevention. General recommendations on immunization: recommendations of the Advisory Committee on Immunization Practices and the American Academy of Family Physicians. MMWR 2002;51 (No. RR-2):6-7.
4. Thornton JG, Page C, Foote G, Arthur GR, Tovey LAD, Scott JS. Efficacy and long term effects of antenatal prophylaxis with anti-D immunoglobulin. Br Med J. 1989;298:1671-1673.
5. Stucki M, Moudry R, Kempf C, Omar A, Schlegel A, Lerch PG. Characterisation of a chromatographically produced anti-D immunoglobulin product. J Chromatogr B. 1997;700:241-248.
6. Horowitz B, Chin S, Prince AM, Brotman B, Pascual D, Williams B. Preparation and characterization of S/D-FFP, a virus sterilized "fresh frozen plasma". J Thromb Haemost. 1991;65:1163.
7. Horowitz B, Bonomo R, Prince AM, Chin S, Brotman B, Shulman RW. Solvent/detergent-treated plasma: a virus-inactivated substitute for fresh frozen plasma. Blood. 1992;79:826-831.
8. Lazarus AH, Crow AR. Mechanism of action of IVIG and anti-D in ITP. Transfus Apher Sci. 2003;28:249-255.
9. Bichler J, Schöndorfer G, Pabst G, Andresen I. Pharmacokinetics of anti-D IgG in pregnant RhD-negative women. BJOG. 2003;110:39-45.
10. Ware RE, Zimmerman SA. Anti-D: mechanisms of action. Semin Hematol. 1998;35:14-22.
11. MacKenzie IZ, Bichler J, Mason GC, et al. Efficacy and safety of a new, chromatographically purified rhesus (D) immunoglobulin. Eur J Obstetr Gynecol Reprod Biol. 2004;117:154-161.

16 HOW SUPPLIED/STORAGE AND HANDLING

- RHOPHYLAC 1500 IU (300 mcg) is supplied in packages of one or ten (10) single-dose, prefilled, ready-to-use, glass syringe(s), each containing 2 mL liquid for injection. Each syringe is accompanied by a SafetyGlide™ needle for intravenous or intramuscular use.

Each product presentation includes a package insert and the following components:

Table 7. How Supplied
Presentation | Carton NDC Number | Components
1500 IU (300 mcg) | 44206-300-01 | - Single-dose, prefilled 2 mL syringe [NDC 44206-300-90] - SafetyGlide needle
1500 IU (300 mcg) Multipack | 44206-300-10 | - Ten single-dose, prefilled 2 mL syringes [NDC 44206-300-90] - Ten SafetyGlide needles

Storage and Handling

- DO NOT FREEZE.
- RHOPHYLAC contains no preservatives; do not store at room temperature.
- Store at 2 to 8°C (36 to 46°F) for a shelf life of 36 months from the date of manufacture, as indicated by the expiration date printed on the outer carton and syringe label.
- Keep RHOPHYLAC in its original carton to protect it from light.
- The RHOPHYLAC prefilled syringe is not made with natural rubber latex.
- Discard any unused product and all used disposable supplies.

17 PATIENT COUNSELING INFORMATION

Please inform patients of the following:

- Immediately report the following signs and symptoms to their physician: hives, chest tightness, wheezing, hypotension, and anaphylaxis [see Warnings and Precautions (5.1)].
- RHOPHYLAC is made from human blood and may contain infectious agents that can cause disease (e.g., viruses and, theoretically, the CJD agent). Explain that the risk RHOPHYLAC may transmit an infectious agent has been reduced by screening all plasma donors, by testing the donated plasma for certain viruses, and by inactivating and/or removing certain viruses during manufacturing. Advise patients to report any symptoms that concern them and that may be related to viral infections [see Warnings and Precautions (5.3)].
- RHOPHYLAC may interfere with the response to live virus vaccines (e.g., measles, mumps, rubella, and varicella), and instruct them to notify their healthcare professional of this potential interaction when they are receiving vaccinations.
- Receiving the antepartum dose of RHOPHYLAC for suppression of Rh isoimmunization will need a second dose within 72 hours of birth if the baby's blood type is Rh-positive.
- Patients being treated with RHOPHYLAC for ITP to immediately report symptoms of intravascular hemolysis, including back pain, shaking chills, fever, discolored urine, decreased urine output, sudden weight gain, edema, and/or shortness of breath [see Warnings and Precautions (5.4)].

Manufactured by:
CSL Behring AG
Bern, Switzerland
US License No. 1766

Distributed by:
CSL Behring LLC
Kankakee, IL 60901 USA

Planova® is a registered trademark of Asahi Kasei Medical Co., Ltd.
SafetyGlide™ is a trademark of Becton, Dickinson and Company

PRINCIPAL DISPLAY PANEL - 300 mcg Syringe Carton - 44206-300-01

NDC 44206-300-01

300 mcg

Rh₀(D) Immune Globulin Intravenous (Human)

Rhophylac®

1500 IU

For Intravenous or Intramuscular Injection. Rx only

CSL Behring

PRINCIPAL DISPLAY PANEL - 300 mcg Syringe Carton - 44206-300-10

NDC 44206-300-10

300 mcg

Rh₀(D) Immune Globulin
Intravenous (Human)

Rhophylac®

1500 IU

For Intravenous or Intramuscular Injection.

Rx only

CSL Behring